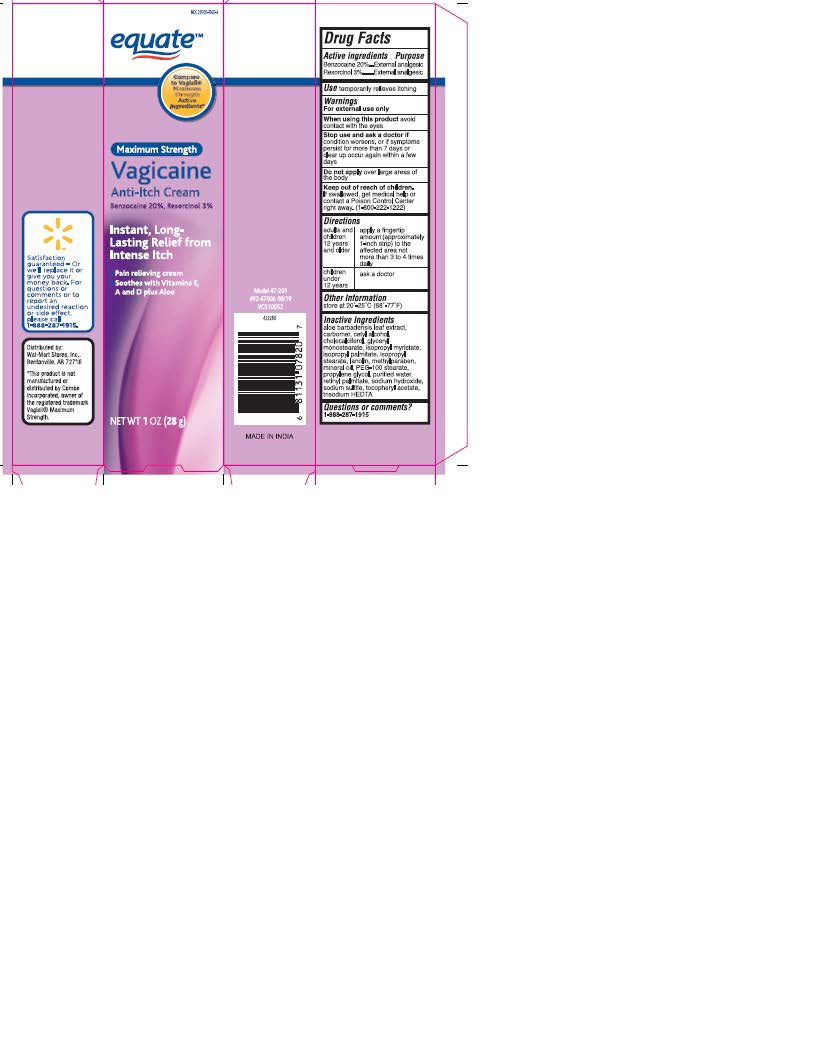 DRUG LABEL: Vagicaine
NDC: 29500-7820 | Form: CREAM
Manufacturer: Personal Care Products, Inc.
Category: otc | Type: HUMAN OTC DRUG LABEL
Date: 20230103

ACTIVE INGREDIENTS: BENZOCAINE 5.67 g/28 g; RESORCINOL 0.85 g/28 g
INACTIVE INGREDIENTS: ALOE VERA LEAF; CARBOMER HOMOPOLYMER TYPE C (ALLYL PENTAERYTHRITOL CROSSLINKED); CETYL ALCOHOL; CHOLECALCIFEROL; GLYCERYL MONOSTEARATE; ISOPROPYL MYRISTATE; ISOPROPYL PALMITATE; ISOPROPYL STEARATE; LANOLIN; METHYLPARABEN; MINERAL OIL; PEG-100 STEARATE; PROPYLENE GLYCOL; WATER; VITAMIN A PALMITATE; SODIUM HYDROXIDE; SODIUM SULFITE; .ALPHA.-TOCOPHEROL ACETATE; TRISODIUM HEDTA

Drug Facts Active ingredients

Benzocaine 20%
Resorcinol 3%

Purpose

External analgesic

Keep out of reach of children

If swallowed, get medical help or contact a Poison Control Center right away. (1-800-222-1212)

Use

temporarily relieves itching

Warnings

For external use only

When using this product

avoid contact with the eyes

Stop use and ask a doctor if

condition worsens, or if symptoms persist for more than7 days or clear up and occur again within a few days

Do not apply Directions

Do not apply over large area of the body.

adults and children 12 years and older apply a fingertip amount (approximately 1-inch strip) to the affected area not more than 3 to 4 times daily

children under 12 years ask a doctor

Other Information

store at 20° -25° C (68° -77° F)

Inactive Ingredients

aloe barbadensis leaf extract, carbomer, cetyl alcohol, cholecalciferol, glyceryl monostearate, isopropyl myristate, isopropyl palmitate, isopropyl sterate, lanolin, methylparaben, mineral iol, PEG-100 stearate, propylene glycol, purified water, retinyl palmitate, sodium hydroxide, sodium sulfite, tocopheryl acetate, trisodium HEDTA

Questions or comments?

1-888-287-1915

Vagicaine Product Label

equate™

Compare to Vagisil Maxium Strength Active Ingredients ®

Maxium Strength

Vagicaine
Anti-Itch Cream
Bennzocaine 20%, Resorcinol 3%

Instant, Long-Lasting Relief from Intense Itch

Pain relieving cream
Soothes with Vitamins E, A and D plus Aloe

NET T 1 OZ(28 g)

Satisfaction guaranteed - Or we'll replace it or give you your money back. For questions or comments or to report an undesired reaction or side effect, please call 1-888-287-1915

distributed by:

Wal-Mart Stores, Inc.

Bentonville, AR 7276

*This product is not manufactured or distributed by Combe Incorporated, owner of the registered trade mark Vagisil® Maxium Strength.